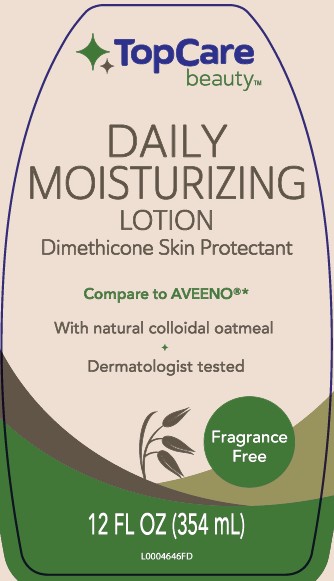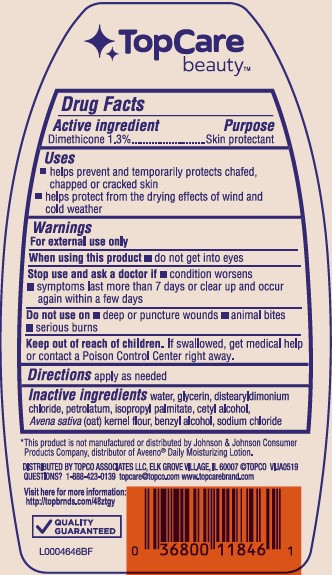 DRUG LABEL: Daily Moisturizing
NDC: 36800-619 | Form: LOTION
Manufacturer: Topco Associates LLC
Category: otc | Type: HUMAN OTC DRUG LABEL
Date: 20260213

ACTIVE INGREDIENTS: DIMETHICONE 13.13 mg/1 mL
INACTIVE INGREDIENTS: WATER; GLYCERIN; DISTEARYLDIMONIUM CHLORIDE; PETROLATUM; ISOPROPYL PALMITATE; CETYL ALCOHOL; OATMEAL; BENZYL ALCOHOL; SODIUM CHLORIDE

Top Care 619.003/619AC rev 2
Daily Moisturizing Lotion

Claim

TopCare

beauty

Active ingredient

Dimethicone 1.3%

Purpose

Skin Protectant

Uses

- helps prevent and temporarily protects chafed, chapped or cracked skin
- helps protect from the drying effects of wind and cold weather

Warnings

For external use only

When using this product

- do not get into eyes

Stop use and ask a doctor if

- condition worsens
- symptoms last more than 7 days or clear up and occur again within a few days

Do not use on

- deep or puncture wounds
- animal bites
- serious burns

Keep out of reach of children.

If swallowed, get medical help or contact a Poison Control Center right away.

Directions

apply as needed

Inactive ingredients

water, glycerin, distearyldimonium chloride, petrolatum, isopropyl palmitate, cetyl alcohol, Avena sativa (oat) kernel flour, benzyl alcohol, sodium chloride

ADVERSE REACTION

*This product is not manufactured or distributed by Johnson & Johnson Consumer Products Company, distributor of Aveeno®Daily Moisturizing Lotion

DISTRIBUTED BY TOPCO ASSOCIATES LLC

ELK GROVE VILLAGE, IL 60007 ©TOPCO VIJA0519

QUESTIONS? 1-888-423-0139 topcare@topco.com www.topccarebrand.com

Visit here for more information:

http://topbrnds.com/48ztgy

QUALITY GUARANTEED

principal display panel

TOPCARE

beauty™

DAILY MOISTURIZING LOTION

Dimethicone Skin Protectant

Compare to AVEENO®*

With natural colloidal oatmeal

Dermatologist tested

Fragrance Free

12 FL OZ (354 mL)